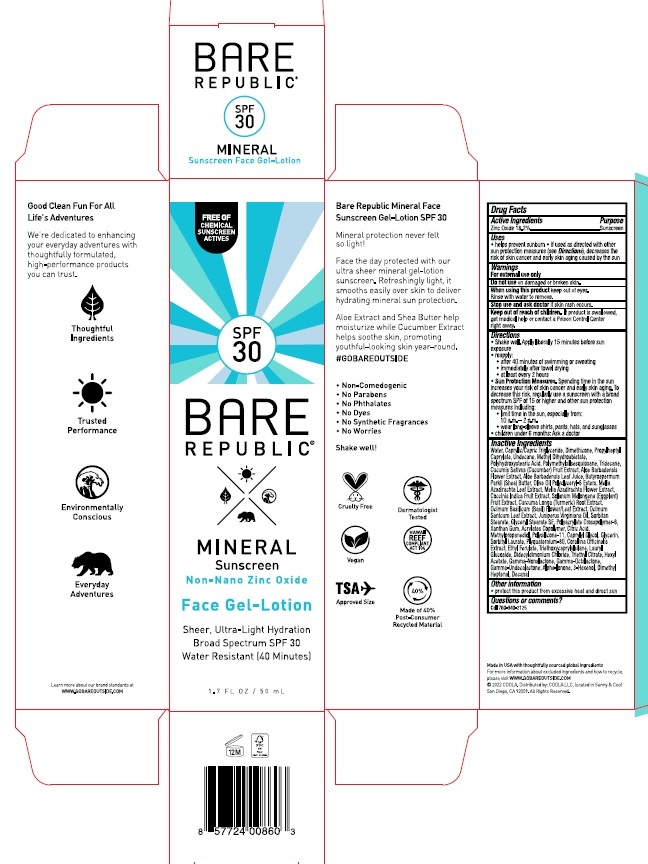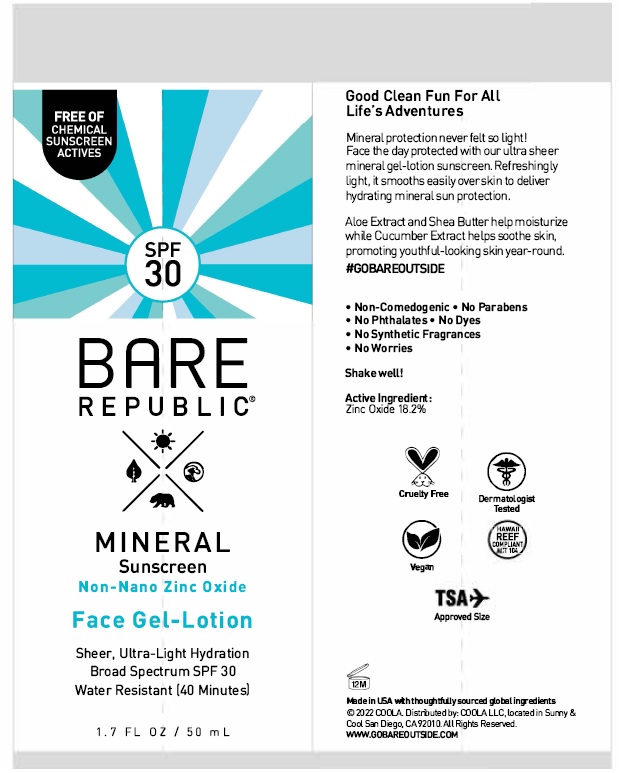 DRUG LABEL: Coola Bare Republic Mineral Face Gel-Lotion
NDC: 79753-043 | Form: LOTION
Manufacturer: COOLA LLC
Category: otc | Type: HUMAN OTC DRUG LABEL
Date: 20231220

ACTIVE INGREDIENTS: ZINC OXIDE 18.2 g/100 mL
INACTIVE INGREDIENTS: WATER; MEDIUM-CHAIN TRIGLYCERIDES; DIMETHICONE; PROPYLHEPTYL CAPRYLATE; UNDECANE; METHYL DIHYDROABIETATE; POLYHYDROXYSTEARIC ACID (2300 MW); POLYMETHYLSILSESQUIOXANE (4.5 MICRONS); TRIDECANE; CUCUMBER; ALOE VERA FLOWER; ALOE VERA LEAF; SHEA BUTTER; OLIVE OIL POLYGLYCERYL-6 ESTERS; AZADIRACHTA INDICA LEAF; AZADIRACHTA INDICA FLOWER; COCCINIA GRANDIS FRUIT; EGGPLANT; TURMERIC; OCIMUM BASILICUM FLOWERING TOP; HOLY BASIL LEAF; JUNIPERUS VIRGINIANA OIL; SORBITAN MONOSTEARATE; GLYCERYL STEARATE SE; AMMONIUM ACRYLOYLDIMETHYLTAURATE, DIMETHYLACRYLAMIDE, LAURYL METHACRYLATE AND LAURETH-4 METHACRYLATE COPOLYMER, TRIMETHYLOLPROPANE TRIACRYLATE CROSSLINKED (45000 MPA.S); XANTHAN GUM; BUTYL ACRYLATE/METHYL METHACRYLATE/METHACRYLIC ACID COPOLYMER (18000 MW); CITRIC ACID MONOHYDRATE; METHYLPROPANEDIOL; DIMETHICONE/VINYL DIMETHICONE CROSSPOLYMER (SOFT PARTICLE); CAPRYLYL GLYCOL; GLYCERIN; SORBITYL LAURATE; CORALLINA OFFICINALIS; ETHYL FERULATE; TRIETHOXYCAPRYLYLSILANE; LAURYL GLUCOSIDE; DIDECYLDIMONIUM CHLORIDE; TRIETHYL CITRATE; HEXYL ACETATE; .GAMMA.-NONALACTONE; .GAMMA.-OCTALACTONE; .GAMMA.-UNDECALACTONE; .ALPHA.-IONONE; 3-HEXEN-1-OL, (3Z)-; 2,6-DIMETHYL-5-HEPTENAL; DECANAL

Coola Bare Republic Mineral Face Gel-Lotion SPF 30

Drug Facts

Active Ingredients

Zinc Oxide 18.2%

Purpose

Suncreen

INDICATIONS AND USAGE

Uses • helps prevent sunburn • if used as directed with other sun protection measures

(see Directions), decreases the risk of skin cancer and early skin aging caused by the sun

Warnings

For external use only

Do not use on damaged or broken skin

When using this product keep out of eyes. Rinse with water to remove.

Stop use and ask doctor if skin rash occurs

Keep out of reach of children. If product is swallowed, get medical help or

contact a Poison Control Center right away.

Directions
● Shake well. Apply liberally 15 minutes before sun exposure
● reapply:
● after 40 minutes of swimming or sweating
● immediately after towel drying
● at least every 2 hours
● Sun Protection Measures. Spending time in the sun
increases your risk of skin cancer and early skin aging. To
decrease this risk, regularly use a sunscreen with a broad
spectrum SPF of 15 or higher and other sun protection
measures including:
● limit time in the sun, especially from:
10 a.m. - 2 p.m.
● wear long-sleeve shirts, pants, hats, and sunglasses
● Children under 6 months: Ask a doctor

Inactive Ingredients

Water, Caprylic/Capric Triglyceride, Dimethicone, Propylheptyl
Caprylate, Undecane, Methyl Dihydroabietate,
Polyhydroxystearic Acid, Polymethylsilsesquioxane, Tridecane,
Cucumis Sativus (Cucumber) Fruit Extract, Aloe Barbadensis
Flower Extract, Aloe Barbadensis Leaf Juice, Butyrospermum
Parkii (Shea) Butter, Olive Oil Polyclyceryl-6 Esters, Melia
Azadirachta Leaf Extract, Melia Azadirachta Flower Extract,
Coccinia Indica Fruit Extract, Solanum Melongena (Eggplant)
Fruit Extract, Curcuma Longa (Turmeric) Root Extract,
Ocimum Basilicum (Basil) Flower/Leaf Extract, Ocimum
Santcum Leaf Extract, Juniperus Virginiana Oil, Sorbitan
Stearate, Glyceryl Stearate SE, Polyacrylate Crosspolymer-6,
Xanthan Gum, Acrylates Copolymer, Citric Acid,
Methlpropanediol, Polysilicone-11, Caprylyl Glycol, Glycerin,
Sorbityl Laurate, Plyquaternium-80, Corallina Officinalis
Extract, Ethyl Ferulate, Triethoxycaprylylsilane, Lauryl
Glucoside, Didecyldimonium Chloride, Triethyl Citrate, Hexyl
Acetate, Gamma-Nonalactone, Gamma-Octalactone,
Gamma-Undecalactone, Alpha-Ionone, 3-Hexenol, Dimethyl
Heptenal, Decanal

Other information

- protect this product from excessive heat and direct sun

Questions or comments?
Call 760-940-2125

COOLA Label

SPF

30

BARE

REPUBLIC

MINERAL

Sunscreen

Non-Nano Zinc Oxide

Face Gel-Lotion

Sheer, Ultra-Light Hydration

Broad Spectrum SPF 30

Water Resistant (40 Minutes)

1.7 FL OZ / 50 mL

©2022 COOLA. Distributed by: COOLA LLC, located in Sunny & Cool

San Diego, CA 92009.

WWW.GOBAREOUTSIDE.COM

res